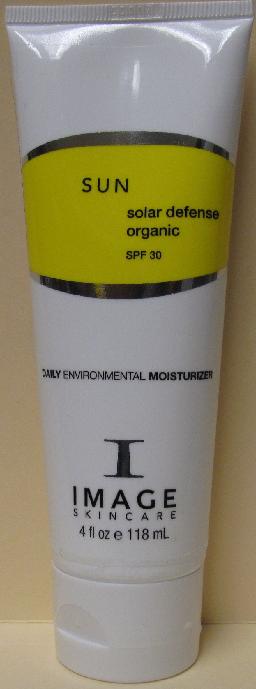 DRUG LABEL: SUN Solar Defense Organic SPF30
NDC: 62742-4038 | Form: CREAM
Manufacturer: Allure Labs, Inc.
Category: otc | Type: HUMAN OTC DRUG LABEL
Date: 20100701

ACTIVE INGREDIENTS: ZINC OXIDE 190 mg/1 mL

Drug Facts

Active Ingredients:

Zinc Oxide

Purpose:

Sunscreen

Uses:

- An organic UVA/UVB broad spectrum daily moisturizer. Provides ultimate protection against the aging effects of the sun and other environmental exposures. Enriched with essential vitamins and anti-oxidants that prevent free radical damage and preserving skin hydration for the entire day.

- Water Resistant
- Paraben Free

- Chemical free

Directions:
Apply liberally 15-30minute prior to sun exposure. Reapply after prolonged swimming or vigorous activity.
Indications:
Sensitive skin highly exposed to sun

Warnings:

For external use only

When using this product

- Keep out of eyes. If contact occurs rinse with water.
- Discontinue use if irritation or redness occurs

Keep out of reach of children

Inactive Ingredients:

Water (Aqua), Cyclomethicone, Glycrin, Glyceryl Stearate (and) PEG 100 Stearate, Sorbitol, Imperata Cylindrica Root Extract, Polyacrylamide and C13-14 Isoparaffin and Laureth-7, Caprylyl Glycol and Phenoxyethanol and Hexylene Glycol, Lecithin, Ascorbyl Palmitate (Vitramin C), Xanthan Gum, Dipotassium Glyrhhizate, Olea Europea (Olive) Leaf Extract, Disodium EDTA.

PACKAGE LABEL

Distributor:

Image International

Palm Beach, FL 33411 USA

www.imageskincare.com

Image of the product: